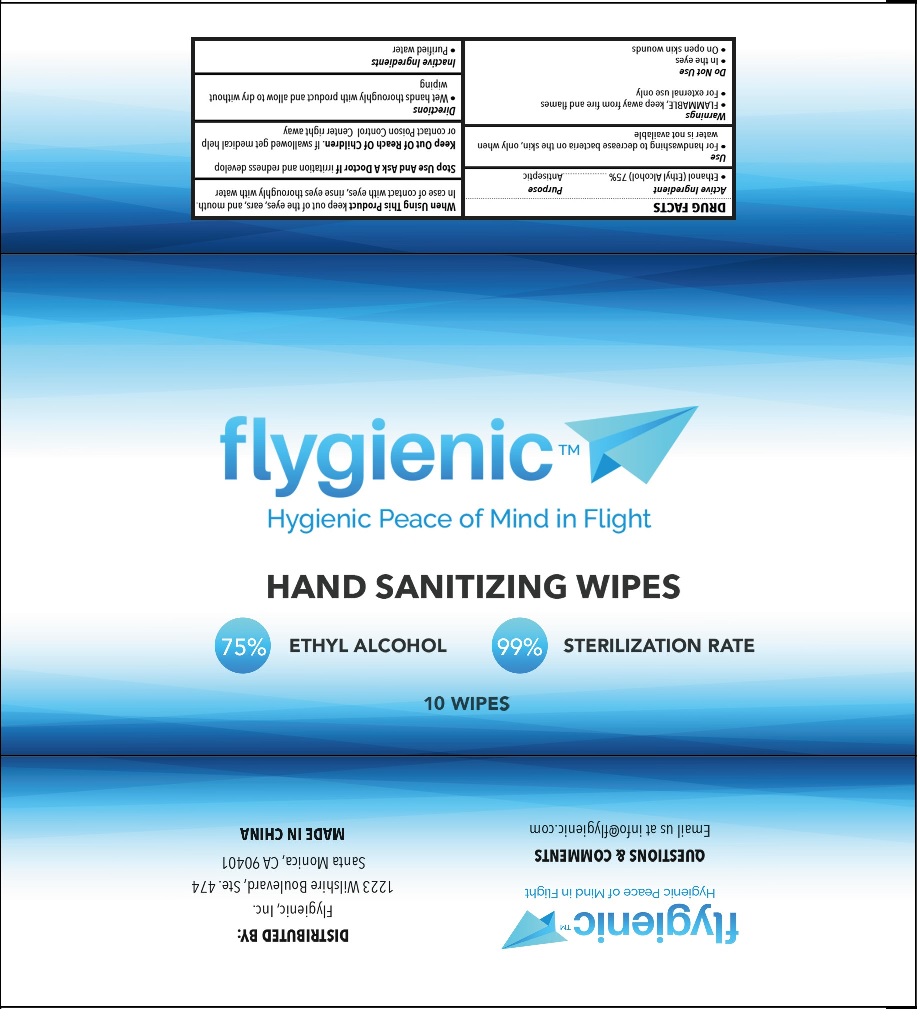 DRUG LABEL: Hand Sanitizing Wipes
NDC: 77435-023 | Form: CLOTH
Manufacturer: HAINING LILY CLEANING PRODUCTS CO., LTD
Category: otc | Type: HUMAN OTC DRUG LABEL
Date: 20210329

ACTIVE INGREDIENTS: ALCOHOL 75 g/100 g
INACTIVE INGREDIENTS: WATER

Wipes

Active Ingredient

Ethanol (Ethyl Alcohol) ..... 75%

Purpose

Antiseptic

USE

- For handwashing to decrease bacteria on the skin, only when water is not available.

Warning

- Flammable, keep away from fire or flame.
- For external use only.

Do not use

- In the eyes
- On open skin wounds

When Using This Product

Keep out of the eyes, ears and mouth. In case of contact with eyes, rinse eyes thoroughly with water.

Stop use and ask a doctor, if irritaion and redness develop.

KEEP OUT OF REACH OF CHILDREN

●If swallowed, get medical help or contact a Poison Contrl Center right away.

Directions

- Wet hands thoroughluy with produt and allow to dry without wiping.

Inactive ingredients

Purified Water